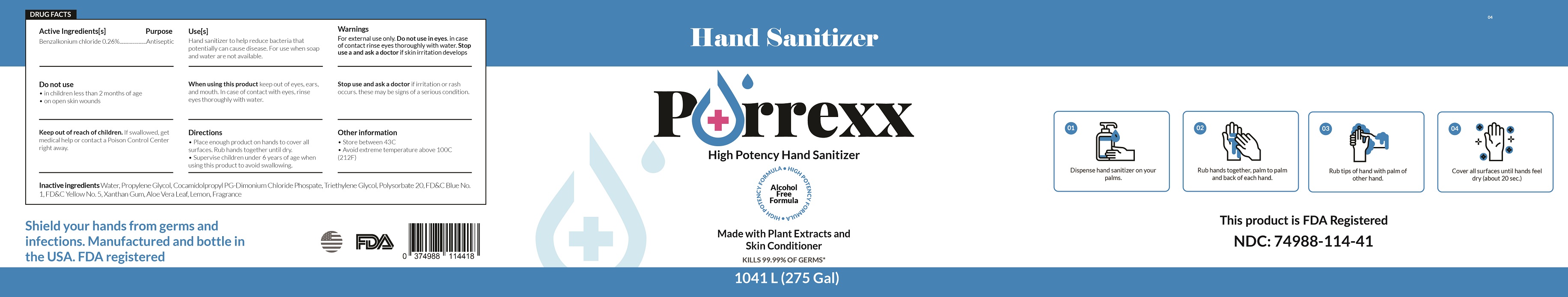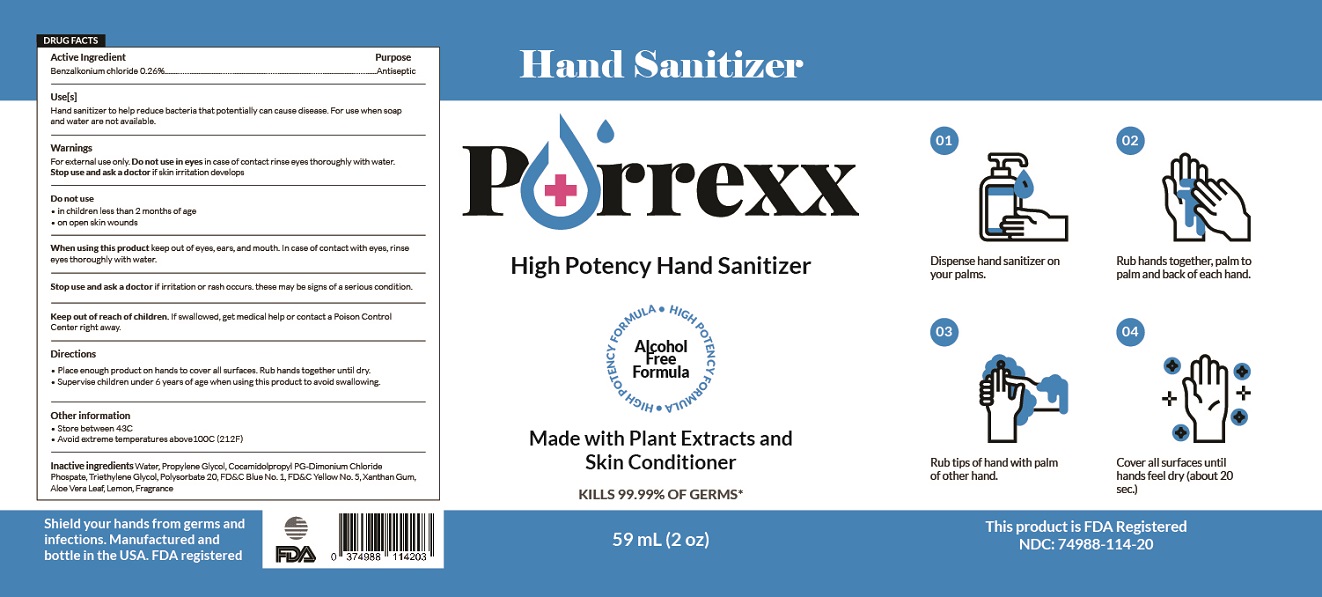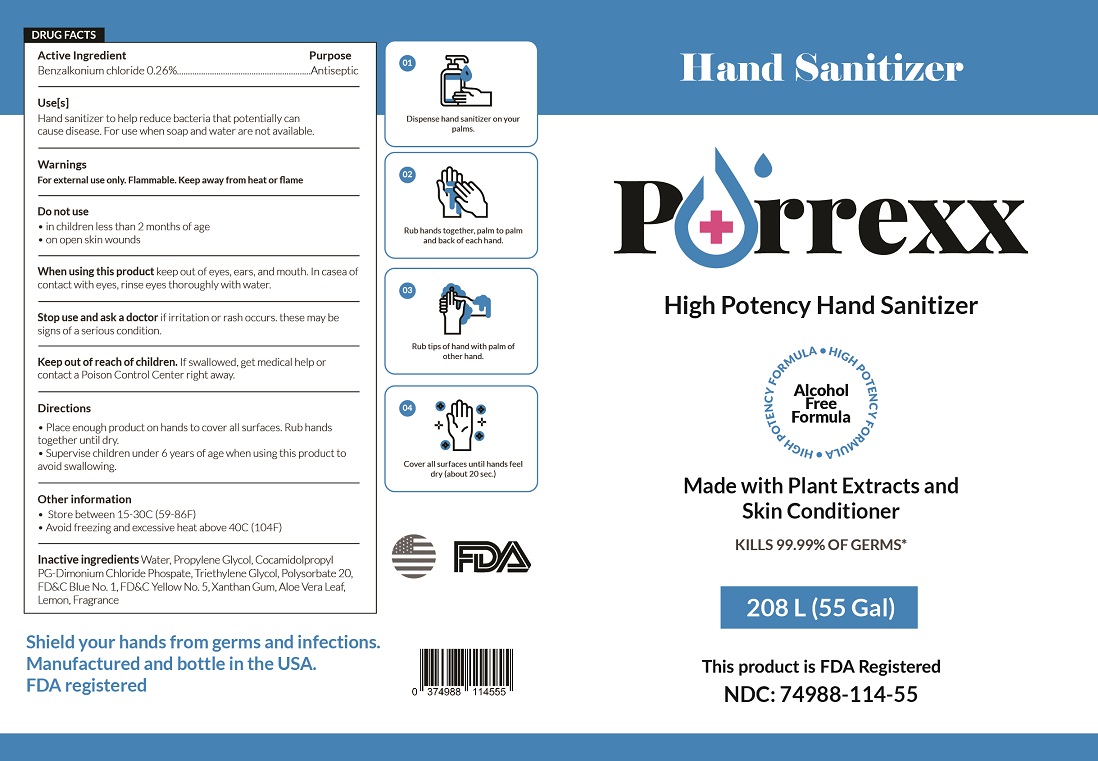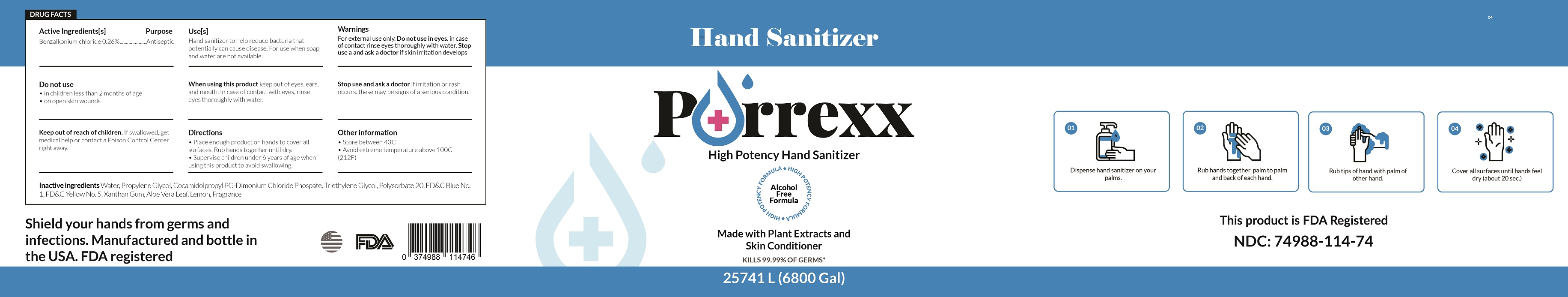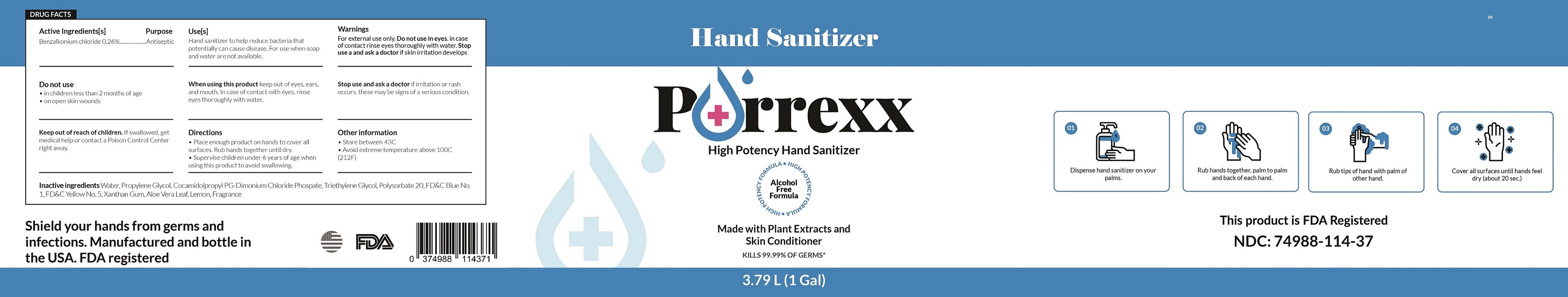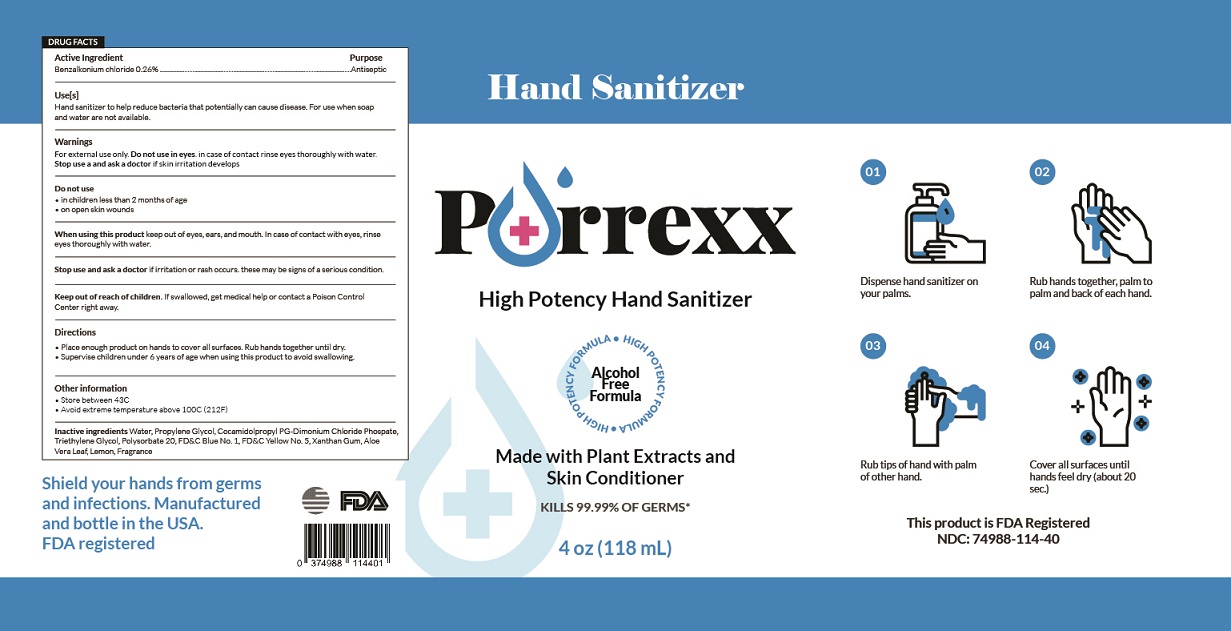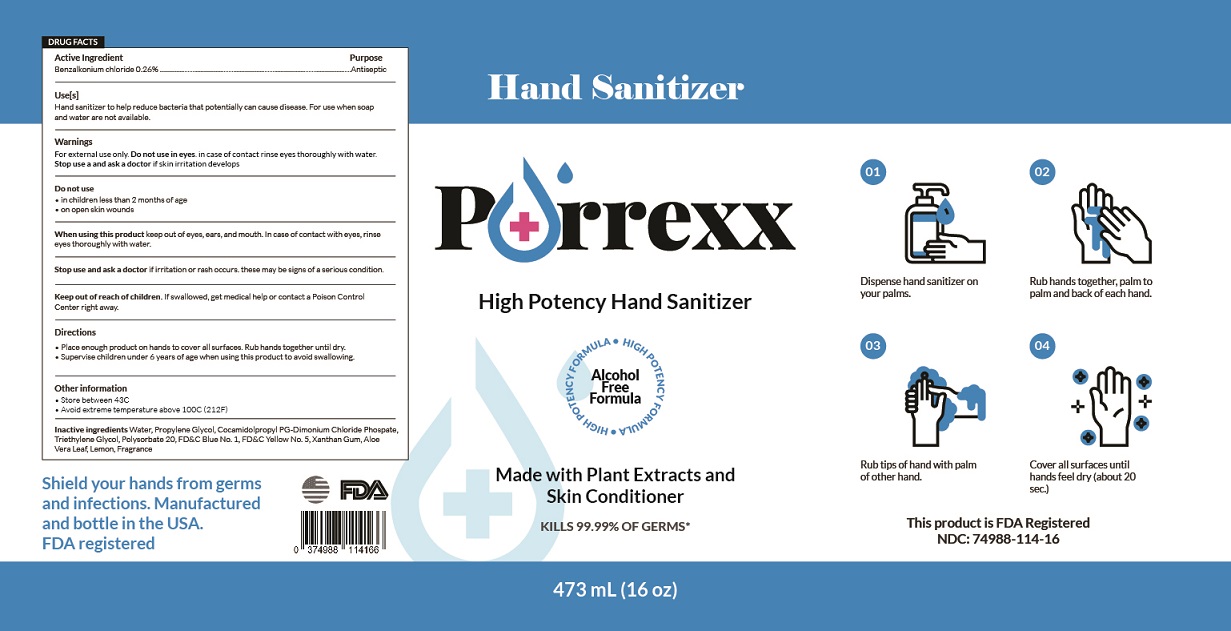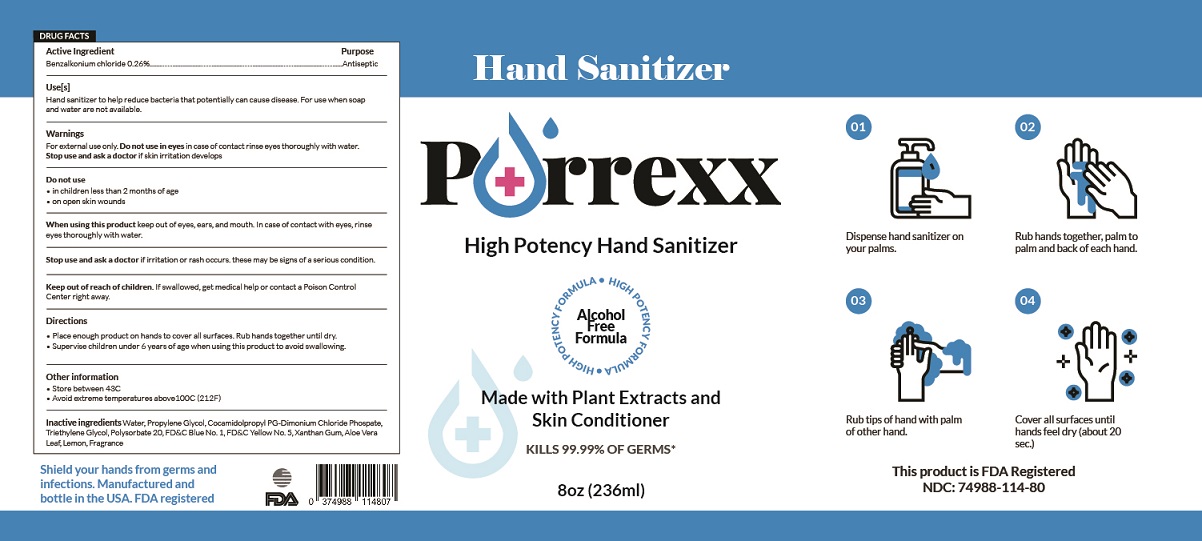 DRUG LABEL: Hand Sanitizer
NDC: 74988-114 | Form: GEL
Manufacturer: SanitizeNow Inc.
Category: otc | Type: HUMAN OTC DRUG LABEL
Date: 20200617

ACTIVE INGREDIENTS: BENZALKONIUM CHLORIDE 0.13 g/100 mL
INACTIVE INGREDIENTS: COCAMIDOPROPYL PG-DIMONIUM CHLORIDE PHOSPHATE; PROPYLENE GLYCOL; TRIETHYLENE GLYCOL; POLYSORBATE 20; FD&C YELLOW NO. 5; XANTHAN GUM; LEMON; WATER; ALOE VERA LEAF; FD&C BLUE NO. 1

Disclaimer: Most OTC drugs are not reviewed and approved by FDA, however they may be marketed if they comply with applicable regulations and policies. FDA has not evaluated whether this product complies.

The hand sanitizer is manufactured using only the following ingredients in the preparation of the product:

Benzalkonium Chloride 0.26%
Propylene Glycol
Cocamidolpropyl PG-Dimonium Chloride Phospate
Sterile distilled water or boiled cold water.
Triethylene Glycol
Polysorbate 20
FD&C Blue No. 1
FD&C Yellow No. 5
Xanthan Gum
Aloe Vera Leaf
Lemon
Fragrance

The firm does not add other active or inactive ingredients. Different or additional ingredients may impact the quality and potency of the product.

Active Ingredient(s)

Benzalkonium chloride 0.26% Purpose: Antiseptic

Purpose

Antiseptic, Hand Sanitizer

Use

Hand Sanitizer to help reduce bacteria that potentially can cause disease. For use when soap and water are not available.

Warnings

For external use only.

Do not use

- In children less than 2 months of age
- On open skin wounds
- In eyes. In case of contact, rinse eyes thoroughly with water

When using this product keep out of eyes, ears, and mouth. In case of contact with eyes, rinse eyes thoroughly with water.
Stop use and ask a doctor if irritation or rash occurs. These may be signs of a serious condition.
Keep out of reach of children. If swallowed, get medical help or contact a Poison Control Center right away.

Stop use and ask a doctor if irritation or rash occurs. These may be signs of a serious condition.

Keep out of reach of children. If swallowed, get medical help or contact a Poison Control Center right away.

Directions

- Place enough product on hands to cover all surfaces. Rub hands together until dry.
- Supervise children under 6 years of age when using this product to avoid swallowing.

Other information

Store below 43C
Avoid extreme temperatures above 100C (212F)

Inactive ingredients

Water, Propylene Glycol, Cocamidolpropyl PG-Dimonium Chloride Phospate, Triethylene Glycol, Polysorbate 20, FD&C Blue No. 1, FD&C Yellow No. 5, Xanthan Gum, Aloe Vera Leaf, Lemon, Fragrance

Package Label - Principal Display Panel

59 mL NDC: 74988-114-20

118 mL NDC: 74988-114-40
236 mL NDC: 74988-114-80

473 mL NDC: 74988-114-16

3.79 L NDC: 74988-114-37

208 L NDC: 74988-114-55

1041 L NDC: 74988-114-41

25741 L NDC: 74988-114-74